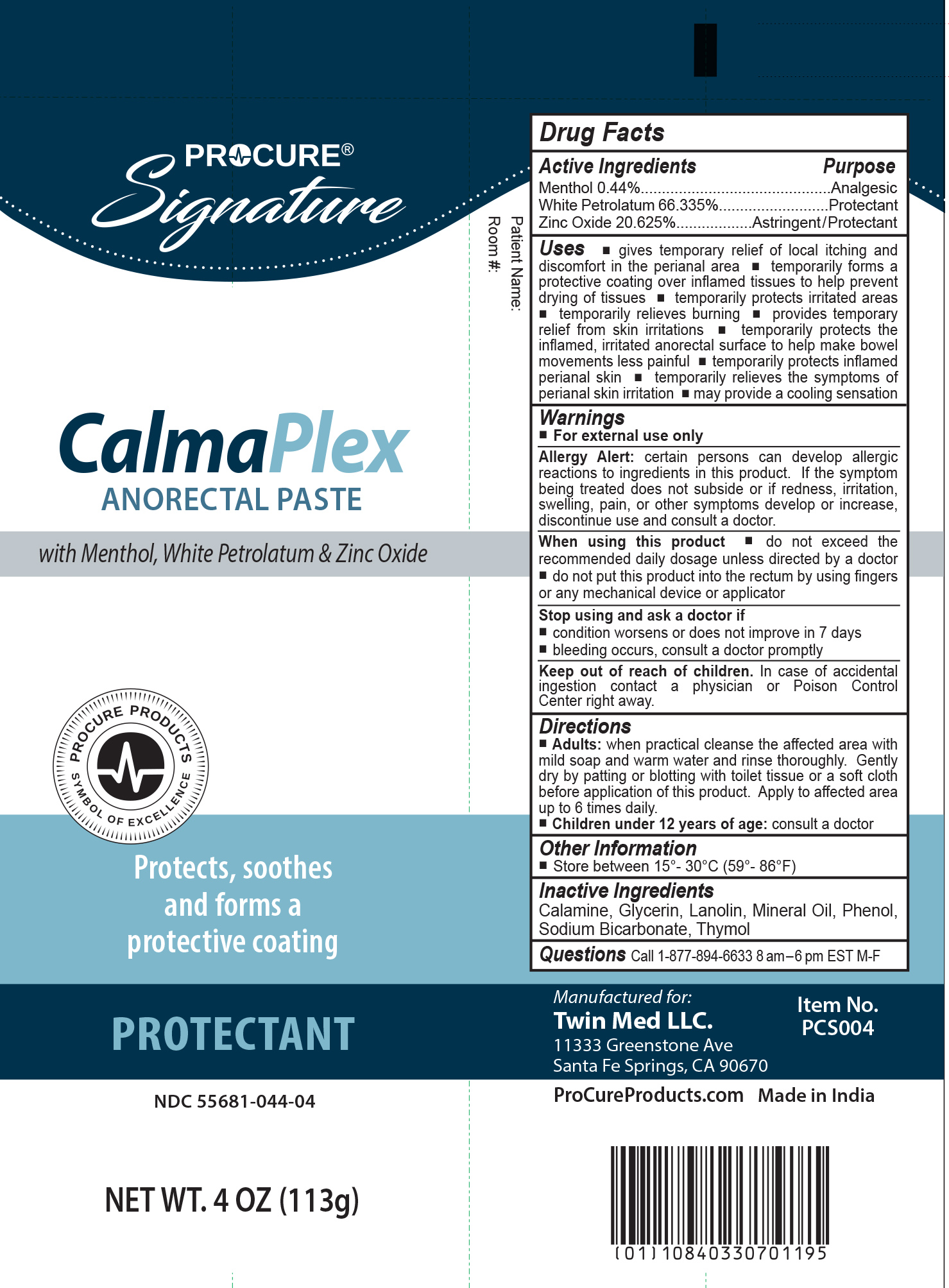 DRUG LABEL: ProCure ClamaPlex
NDC: 55681-044 | Form: OINTMENT
Manufacturer: Twin Med LLC
Category: otc | Type: HUMAN OTC DRUG LABEL
Date: 20251101

ACTIVE INGREDIENTS: WHITE PETROLATUM 66.335 g/100 g; ZINC OXIDE 20.625 g/100 g; MENTHOL 0.44 g/100 g
INACTIVE INGREDIENTS: PHENOL; THYMOL; MINERAL OIL; SODIUM BICARBONATE; FERRIC OXIDE RED; GLYCERIN; LANOLIN

Active Ingredients

Menthol 0.44%

White Petrolatum 66.335%

Zinc Oxide 20.625%

Purpose

Menthol 0.44%.........................................Analgesic

White Petrolatum 66.335%...............................Protectant

Zinc Oxide 20.625%............Astringent / Protectant

Uses

- gives temporary relief of local itching and discomfort in the perianal area
- temporarily forms a protective coating over inflamed tissues to help prevent drying of tissues
- temporarily protects irritated areas
- temporarily relieves burning
- provides temporary relief from skin irritations
- temporarily protects the inflamed, irritated anorectal surface to help make bowel movements less painful
- temporarily protects inflamed perianal skin
- temporarily relieves the symptoms of perianal skin irritation
- may provide a cooling sensation

Warnings

For external use only

Allergy Alert: certain persons can develop allergic reactions to ingredients in this product. If the symptom being treated does not subside or if redness, irritation, swelling, pain, or other symptoms develop or increase, discontinue use and consult a doctor.

When using this product

- do not exceed the recommended daily dosage unless directed by a doctor
- do not put this product into the rectum by using fingers or any mechanical device or applicator

Stop use and ask doctor if

Stop using and ask a doctor if

- condition worsens or does not improve in 7 days
- bleeding occurs, consult a doctor promptly

Keep out of reach of Children. In case of accidental ingestion, contact a physician or Poison Control Center right away.

Directions

- Adults: when practical cleanse the affected area with mild soap and warm water and rinse thoroughly. Gently dry by patting or blotting with toilet tissue or a soft cloth before application of this product. Apply to affected area up to 6 times daily.
- Children under 12 years of age: consult a doctor

Inactive Ingredients

Inactive Ingredients: Calamine, Glycerin, Lanolin, Mineral Oil, Phenol, Sodium Bicarbonate, Thymol